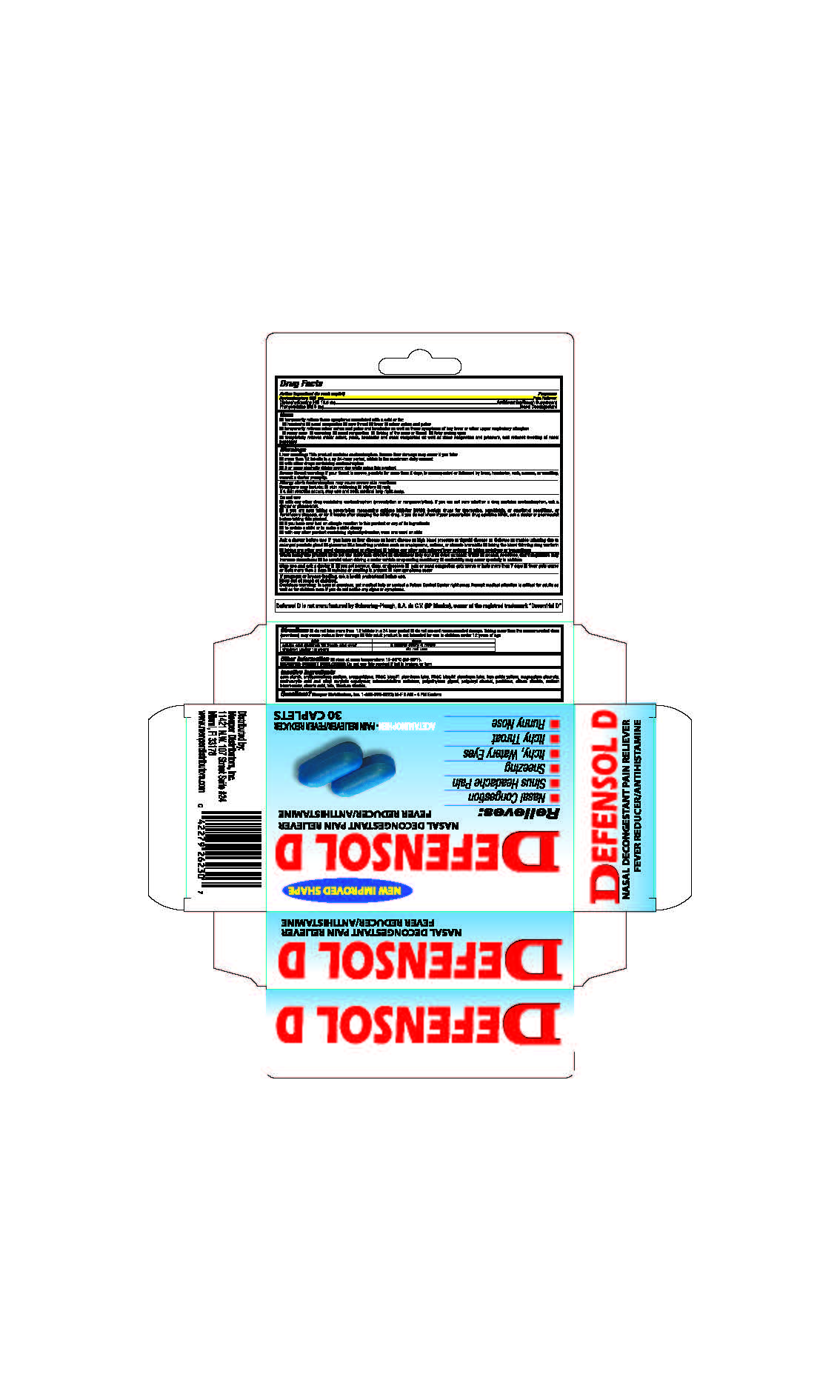 DRUG LABEL: Defensol D Blister Pack
NDC: 53145-009 | Form: TABLET
Manufacturer: Menper Distributors, Inc.
Category: otc | Type: HUMAN OTC DRUG LABEL
Date: 20250722

ACTIVE INGREDIENTS: ACETAMINOPHEN 325 mg/1 1; DIPHENHYDRAMINE HYDROCHLORIDE 12.5 mg/1 1; PHENYLEPHRINE HYDROCHLORIDE 5 mg/1 1
INACTIVE INGREDIENTS: MICROCRYSTALLINE CELLULOSE; SILICON DIOXIDE; POLYETHYLENE GLYCOL, UNSPECIFIED; FD&C BLUE NO. 1; MAGNESIUM STEARATE; POVIDONE; STARCH, PREGELATINIZED CORN; STEARIC ACID; TITANIUM DIOXIDE; SODIUM BICARBONATE; TALC; METHACRYLIC ACID - ETHYL ACRYLATE COPOLYMER (1:2); CROSPOVIDONE; FERRIC OXIDE YELLOW; POLYVINYL ALCOHOL, UNSPECIFIED; CROSCARMELLOSE SODIUM; FD&C BLUE NO. 2

Defensol D Blister Pack

Active ingredients (in each tablet)

Acetaminophen 325 mg

Diphenhydramine HCl 12.5 mg

Phenylephrine HCI 5 mg

Purpose

Pain Reliever

Antihistamine/ Cough Suppresant

Nasal Decongestant

Uses

Temporarily relieves these symptoms associated with cold or flu:

- headache
- nasal congestion
- sore throat
- fever
- minor aches and pains
- Temporarily relieves minor aches, pains, and headache as well as those symptoms of hay fever or other upper respiratory allergies:
- runny nose
- sneezing
- nasal congestion
- itching of the nose or throat
- itchy, watery eyes

Temporarily relieves minor aches, pains, headache, and nasal congestion as well as sinus congestion and pressure, and reduces swelling of nasal passages

Warnings

Liver Warning: This product contains acetaminophen. Severe liver damage may occur if you take

- more than 8 tablets in any 24-hour period, which is the maximum daily amount
- with other drugs containing acetaminophen
- 3 or more alcoholic drinks every day while using this product

Severe throat warning:if sore throat is severe, persists for more than 2 days, is accompanied or followed by fever, headache, rash, nausea, or vomiting, consult a doctor promptly.

Allergy alert: Acetaminophen may cause severe skin reactions:

- Symptoms may include: skin reddening
- blisters
- rash

if a skin reaction occurs, stop use and seek medical help right away.

Do not use

- with any other drug containing acetaminophen (prescription or nonprescription). If you are not sure

whether a drug contains acetaminophen, ask a doctor or pharmacist

- if you are now taking a prescription monoamine oxidase inhibitor (MAOI) (certain drugs for

depression, psychiatric, or emotional conditions, or Parkinson's disease), or for 2 weeks after
stopping the MADI drug. If you do not know if your prescription drug contains MADI, ask a doctor or
pharmacist befaretakingthisprocluct.
■ if you have ever had an allergic reaction to this product or any of its ingredients
■ to sedate a child or to make a child sleepy
■ with any other product containing diphenhydramine, even one used on skin.

Ask doctor before use if you have

- liver desease
- heart disease
- high blood pressure
- thyroid disease
- diabetes
- trouble urinating due to an enlarged prostate gland
- glaucoma
- a breathing problem such as emphysema, asthma, or chronic bronchitis
- taking the blood thinning drug warfarin
- taking any other oral nasal decongestant or stimulant
- taking any other pain relieve/fever reducer
- taking sedatives or tranquilizers

When using this product

- do not use more than directed
- drowsiness may occur
- avoid alcoholic drinks
- alcohol, sedatives, and tranquilizers may increase drowsiness
- be careful when driving a motor vehicle or operating machinery
- excitability may occur in children

Stop use and ask a doctor if

- you get nervous, dizzy, or sleepless
- pain or nasal congestion gets worse or lasts more than 7 days
- fever gets worse or lasts more than 3 days
- redness or swelling is present
- new symptoms occur

PREGNANCY OR BREAST FEEDING

If pregnant or breast-feeding,ask a health professional before use.

Keep out of reach of children.

OVERDOSAGE

Overdose warning:In case of overdose, get medical help or contact a Poison Control Center right away. Prompt medical attention is critical for adults as well as for children even if you do not notice any signs or symptoms.

DOSAGE AND ADMINISTRATION

Directions: do not take more than 12 tablets in a 24 hour period.

- do not exceed recommended dosage. Taking more than the recommended dose (overdose) may cause serious liver damage. This adult product is not intended for use in children under 12 years of age

age | dose
adults and children 12 years and over | 2 tablets every 4 hours
children under 12 years | do not use

Inactive ingredients
corn starch, croscarmellose sodium, crospovidone, FD&C blue#1 aluminum lake, FO&C blue#2 aluminum lake, iron oxide yellow, magnesium stearate, methacrylic acid, and ethyl acrylate copolymer, microcrystalline cellulose, polyethylene glycol, polyvinyl alcohol, povidone, s I con dioxide, sodium bicarbonate, stearic acid, talc, titanium oxide.

QUESTIONS

Questions?Menper Distributors, Inc. 1-800-560-5223; M-F 9 AM - 4 PM Eastern